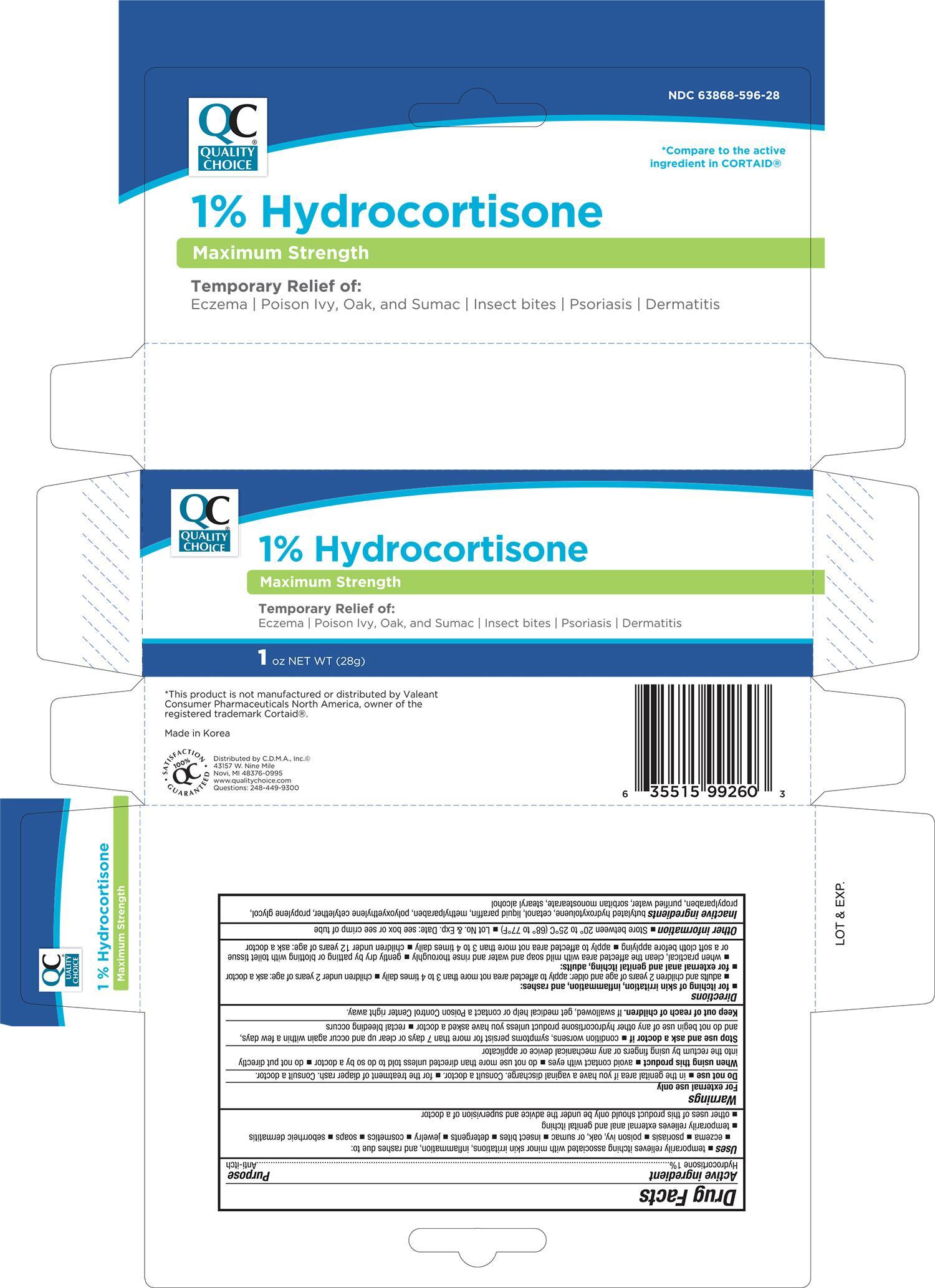 DRUG LABEL: Quality Choice Hydrocortisone Maximum Strength
NDC: 63868-596 | Form: CREAM
Manufacturer: Chain Drug Marketing Association Inc
Category: otc | Type: HUMAN OTC DRUG LABEL
Date: 20191209

ACTIVE INGREDIENTS: HYDROCORTISONE 1 g/100 g
INACTIVE INGREDIENTS: BUTYLATED HYDROXYTOLUENE; PARAFFIN; METHYLPARABEN; PROPYLENE GLYCOL; PROPYLPARABEN; WATER; SORBITAN MONOSTEARATE; STEARYL ALCOHOL

QC Max. Strength Itch Relief Cream 1 oz 99260, 2019

Active ingredient Purpose

Hydrocortisone 1%................................................................... Anti-itch

Uses

- temporarily relieves itching associated with minor skin irritations, inflammation, and rashes due to:
- eczema
- psoriasis
- poison ivy, oak, or sumac
- insect bites
- detergents
- jewelry
- cosmetics
- soaps
- seborrheic dermatitis
- temporarily relieves external anal and genital itching
- other uses of this product should only be under the advice and supervision of a doctor

Warnings

For external use only

Do not use

- in the genital area if you have a vaginal discharge. Consult a doctor.
- for the treatment of diaper rash. Consult a doctor.

When using this product

- avoid contact with eyes
- do not use more than directed unless told to do so by a doctor
- do not put directly into the rectum by using fingers or any mechanical device or applicator

Stop use and ask a doctor if

- conditions worsens, symptoms persist for more than 7 days or clear up and occur again within a few days, and do not begin use of any other hydrocortisone product unless you have asked a doctor
- rectal bleeding occurs

Keep out of reach of children.

If swallowed, get medical help or contact a Poison Control Center right away.

Directions

- for itching of skin irritation, inflammation, and rashes:
- adults and children 2 years of age and older: apply to affected area not more than 3 to 4 times daily
- children under 2 years of age: ask a doctor
- for external anal and genital itching, adults:
- when practical, clean the affected area with mild soap and water and rinse thoroughly
- gently dry by patting or blotting with toilet tissue or a soft cloth before applying
- apply to affected area not more than 3 to 4 times daily
- children under 12 years of age: ask a doctor

Other information

- Store at between 20° to 25°C (68°-77°F)
- Lot No. & Exp. Date: see box or see crimp of tube

Inactive ingredients

butylated hydroxytoluene, cetanol, liquid paraffin, methylparaben, polyoxyethylene cetylether, propylene glycol, propylparaben, purified water, sorbitan monostearate, stearyl alcohol

DOSAGE AND ADMINISTRATION

DISTRIBUTED BY C.D.M.A., INC.

43157 W. NINE MILE

NOVI, MI 48376-0995

www.qualitychoice.com

MADE IN KOREA